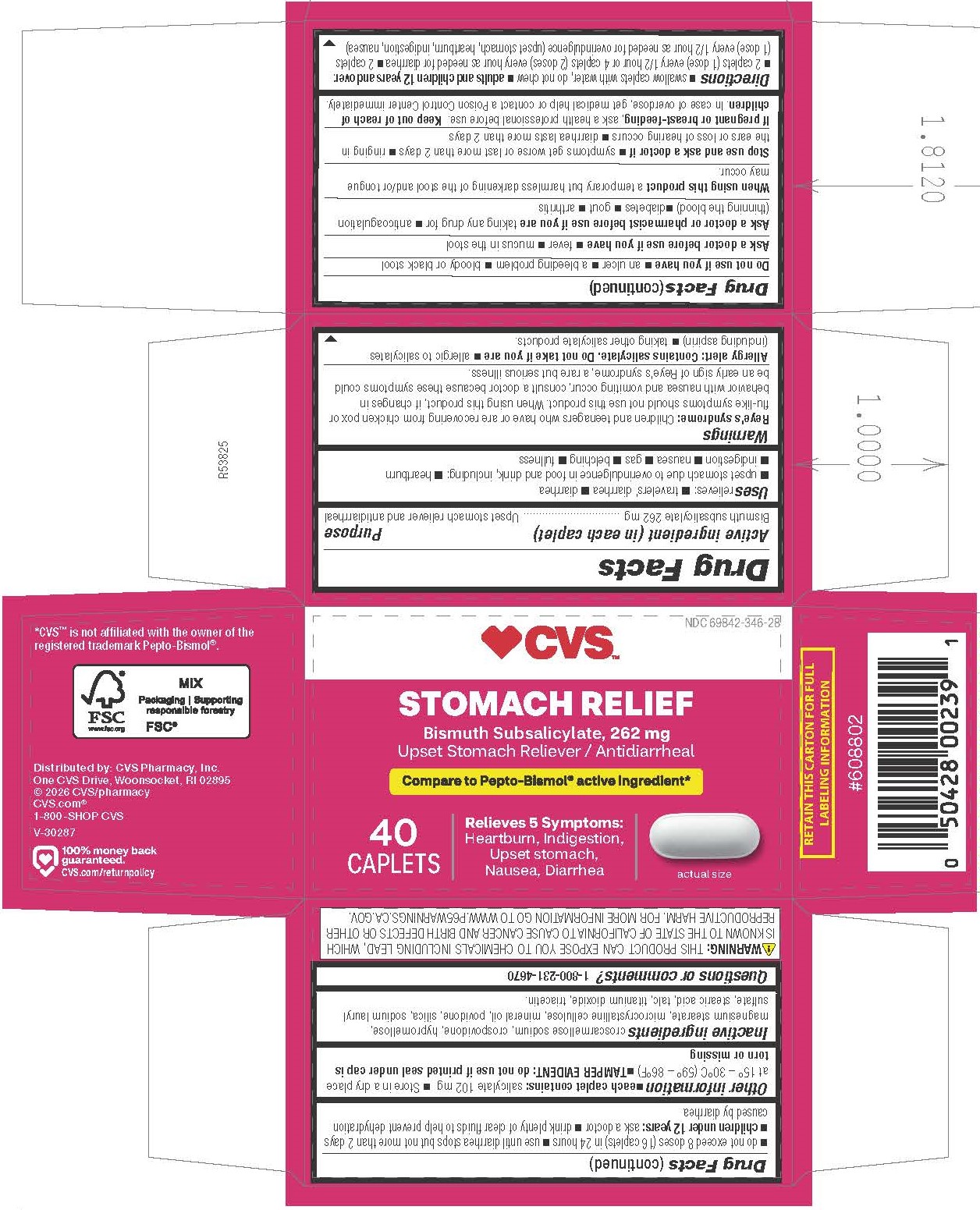 DRUG LABEL: Bismuth Subsalicylate
NDC: 69842-346 | Form: TABLET, FILM COATED
Manufacturer: CVS Pharmacy, Inc.
Category: otc | Type: HUMAN OTC DRUG LABEL
Date: 20260224

ACTIVE INGREDIENTS: BISMUTH SUBSALICYLATE 262 mg/1 1
INACTIVE INGREDIENTS: MAGNESIUM STEARATE; MICROCRYSTALLINE CELLULOSE; SILICON DIOXIDE; TRIACETIN; LIGHT MINERAL OIL; CROSCARMELLOSE SODIUM; CROSPOVIDONE; HYPROMELLOSES; POVIDONE K30; SODIUM LAURYL SULFATE; STEARIC ACID; TALC; TITANIUM DIOXIDE

5346-CVS

Drug Facts

Active ingredient (in each caplet)

Bismuth subsalicylate 262 mg

Purpose

Upset stomach reliever and antidiarrheal

Uses

relieves:

■ travelers’ diarrhea

■ diarrhea

■ upset stomach due to overindulgence in food and drink, including: ■ heartburn ■ indigestion ■ nausea ■ gas ■ belching ■ fullness

WARNINGS

Reye's syndrome: Children and teenagers who have or are recovering from chicken pox or flu-like symptoms should not use this product. When using this product, if changes in behavior with nausea and vomiting occur, consult a doctor because these symptoms could be an early sign of Reye's syndrome, a rare but serious illness.

Allergy alert: Contains salicylate. Do not take if you are

- allergic to salicylates (including aspirin)
- taking other salicylate products.

Do not use if you have

- an ulcer
- a bleeding problem
- bloody or black stool

Ask a doctor before use if you have

- fever
- mucus in the stool

Ask a doctor or pharmacist before use if you are

taking any drug for

- anticoagulation (thinning the blood)
- diabetes
- gout
- arthritis

When using this product

a temporary but harmless darkening of the stool and/or tongue may occur.

Stop use and ask a doctor if

- symptoms get worse or last more than 2 days.
- ringing in the ears or loss of hearing occurs
- diarrhea lasts more than 2 days

PREGNANCY OR BREAST FEEDING

If pregnant or breast-feeding, ask a health professional before use.

Keep out of reach of children.

OVERDOSAGE

In case of overdose, get medical help or contact a Poison Control Center immediately.

Directions

- swallow caplets with water, do not chew
- adults and children 12 years and over: 2 caplets (1 dose) every 1/2 hour or 4 caplets (2 doses) every hour as needed for diarrhea
- 2 caplets (1 dose) every 1/2 hour as needed for overindulgence (upset stomach, heartburn, indigestion, nausea)
- do not exceed 8 doses (16 caplets) in 24 hours
- use until diarrhea stops but not more than 2 days
- children under 12 years: ask a doctor
- drink plenty of clear fluids to help prevent dehydration caused by diarrhea

Other Information

- each caplet contains: salicylate 102 mg
- store in a dry place at 15º - 30º C (59º - 86º F)
- TAMPER EVIDENT: do not use if printed seal under cap is torn or missing

INACTIVE INGREDIENT

croscarmellose sodium, crospovidone, hypromellose, magnesium stearate, microcrystalline cellulose, mineral oil, povidone, silica, sodium lauryl sulfate, stearic acid, talc, titanium dioxide, triacetin.

Questions or comments?

1-800-231-4670

RETAIN THIS CARTON FOR FULL LABELING INFORMATION

*CVS™ is not affiliated with the owner of the registered trademark Pepto-Bismol®.

Distributed by: CVS Pharmacy, Inc.

One CVS Drive, Woonsocket, RI 02895

© 2026 CVS/pharmacy

CVS.com® 1-800-SHOP CVS

V-30287

WARNING: THIS PRODUCT CAN EXPOSE YOU TO CHEMICALS INCLUDING LEAD, WHICH IS KNOWN TO THE STATE OF CALIFORNIA TO CAUSE CANCER AND BIRTH DEFECTS OR OTHER REPRODUCTIVE HARM. FOR MORE INFORMATION GO TO WWW.P65WARNINGS.CA.GOV.

PACKAGE LABEL

CVS™

NDC 69842-346-28

STOMACH RELIEF

Bismuth Subsalicylate, 262 mg

Upset Stomach Reliever/Antidiarrheal

Compare to Pepto-Bismol® active ingredient*

Relieves 5 symptoms:

Heartburn, Indigestion, Upset stomach, Nausea, Diarrhea

40 CAPLETS